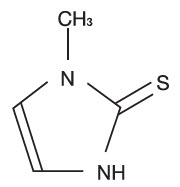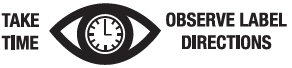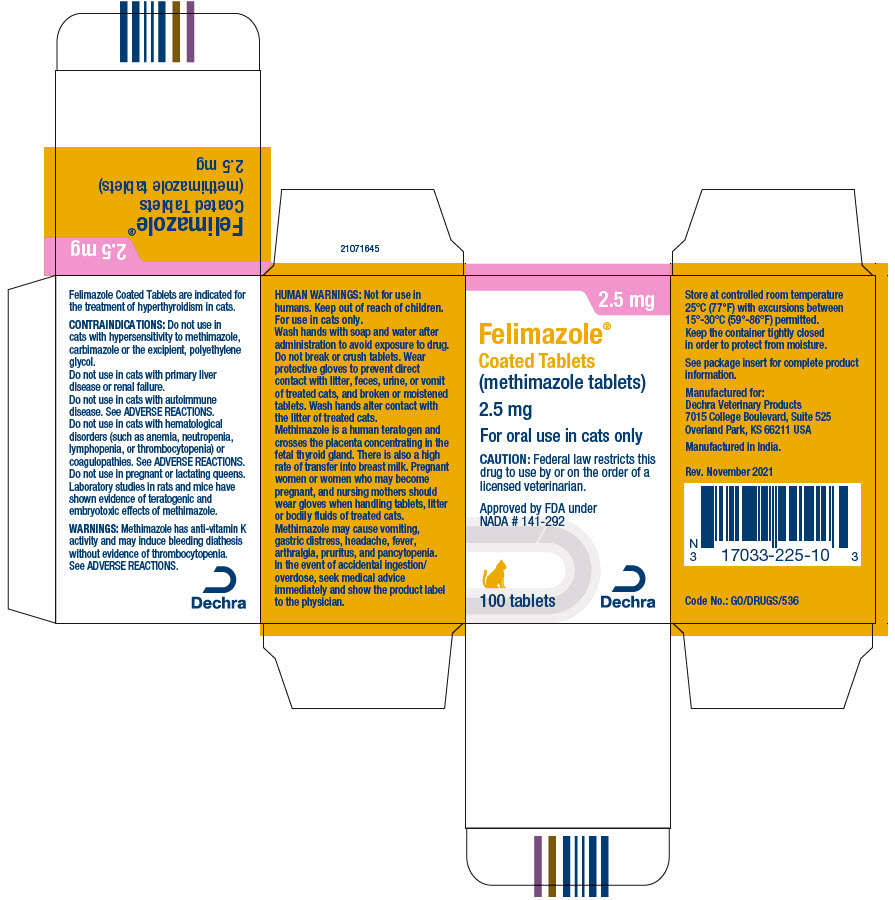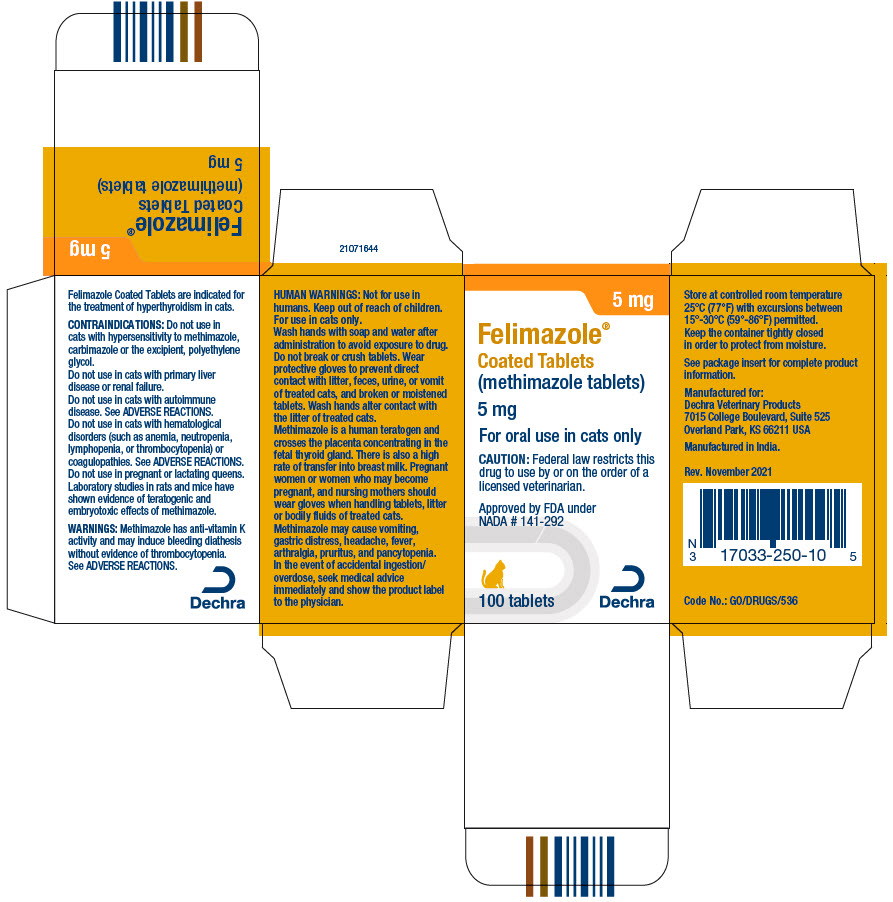 DRUG LABEL: Felimazole
NDC: 17033-225 | Form: TABLET, SUGAR COATED
Manufacturer: Dechra Veterinary Products
Category: animal | Type: PRESCRIPTION ANIMAL DRUG LABEL
Date: 20221222

ACTIVE INGREDIENTS: methimazole 2.5 mg/1 1

Felimazole® Coated Tablets
(methimazole tablets)

For oral use in cats only

CAUTION:

Federal law restricts this drug to use by or on the order of a licensed veterinarian.

DESCRIPTION:

Methimazole is a thioureylene antithyroid drug, which inhibits the synthesis of thyroid hormones. Methimazole (1-methylimidazole-2-thiol) is a white, crystalline substance that is freely soluble in water. The chemical formula is C4H6N2S. Molecular weight is 114.16.

Methimazole Chemical Structure:

VETERINARY INDICATIONS

INDICATION:

Felimazole Coated Tablets (methimazole tablets) are indicated for the treatment of hyperthyroidism in cats.

DOSAGE AND ADMINISTRATION:

The starting dose of Felimazole Coated Tablets is 2.5 mg administered every 12 hours. Following 3 weeks of treatment, the dose should be titrated to effect based on individual serum total T4 (TT4) levels and clinical response. Dose adjustments should be made in 2.5 mg increments. The maximum total dosage is 20 mg per day divided, not to exceed 10 mg as a single administration.

Hematology, biochemistry, and TT4 should be evaluated prior to initiating treatment and monitored after 3 weeks and 6 weeks of treatment. Thereafter, bloodwork should be monitored every 3 months and the dose adjusted as necessary. Cats receiving doses greater than 10 mg per day should be monitored more frequently.

CONTRAINDICATIONS:

Do not use in cats with hypersensitivity to methimazole, carbimazole or the excipient, polyethylene glycol.

Do not use in cats with primary liver disease or renal failure.

Do not use in cats with autoimmune disease. See ADVERSE REACTIONS.

Do not use in cats with hematological disorders (such as anemia, neutropenia, lymphopenia, or thrombocytopenia) or coagulopathies. See ADVERSE REACTIONS.

Do not use in pregnant or lactating queens. Laboratory studies in rats and mice have shown evidence of teratogenic and embryotoxic effects of methimazole.

WARNINGS:

Methimazole has anti-vitamin K activity and may induce bleeding diathesis without evidence of thrombocytopenia. See ADVERSE REACTIONS.

SAFE HANDLING WARNING

HUMAN WARNINGS:

Not for use in humans. Keep out of reach of children. For use in cats only. Wash hands with soap and water after administration to avoid exposure to drug. Do not break or crush tablets. Wear protective gloves to prevent direct contact with litter, feces, urine, or vomit of treated cats, and broken or moistened tablets. Wash hands after contact with the litter of treated cats.

Methimazole is a human teratogen and crosses the placenta concentrating in the fetal thyroid gland. There is also a high rate of transfer into breast milk. Pregnant women or women who may become pregnant, and nursing mothers should wear gloves when handling tablets, litter or bodily fluids of treated cats.

Methimazole may cause vomiting, gastric distress, headache, fever, arthralgia, pruritus, and pancytopenia. In the event of accidental ingestion/overdose, seek medical advice immediately and show the product label to the physician.

PRECAUTIONS:

Use of Felimazole Coated Tablets in cats with renal dysfunction should be carefully evaluated. Reversal of hyperthyroidism may be associated with decreased glomerular filtration rate and a decline in renal function, unmasking the presence of underlying renal disease. Due to potentially serious adverse reactions such as hepatopathy, immune-mediated anemia, thrombocytopenia, and agranulocytosis, cats on methimazole therapy should be monitored closely for any sign of illness including anorexia, vomiting, head/facial pruritus or edema, depression/lethargy, weight loss, anemia, skin lesions, diarrhea, fever, or lymphadenopathy. If a cat becomes ill while on Felimazole Coated Tablets, the drug should be stopped and appropriate hematological and biochemical testing should be done (see ANIMAL SAFETY and POST APPROVAL EXPERIENCE).

Anticoagulants may be potentiated by the anti-vitamin K activity of Felimazole Coated Tablets. Concurrent use of phenobarbital may reduce the clinical effectiveness of Felimazole Coated Tablets.

A reduction in dose of certain drugs (β-adrenergic blocking agents, digitalis glycosides, and theophylline) may be needed when the patient becomes euthyroid.

Methimazole is known to reduce the hepatic oxidation of benzimidazole anthelmintics (e.g. fenbendazole), leading to increased plasma concentration of these anthelmintics when administered concurrently.

Felimazole Coated Tablets caused delayed maturation of the testes in young male cats in the 12-week safety study. See ANIMAL SAFETY. The safety of Felimazole Coated Tablets has not been evaluated in male cats intended for breeding.

ADVERSE REACTIONS:

In a US field study with 113 cats, the most common adverse reactions included change in food consumption (increase or decrease), lethargy, vomiting, diarrhea/loose stool, skin lesions, and abnormal vocalization. Three cats were withdrawn early from the study, one due to unmasking of latent renal disease and two due to the development of skin lesions. Over the course of the study, there was a decreasing trend in the mean counts of red blood cells, lymphocytes, neutrophils and monocytes; however, means remained within or near normal ranges for the testing laboratory.

In the extended use phase of the US field study with 101 cats, the most common adverse reactions reported in the study above (lethargy, anorexia) were also observed. Additional signs occurring more frequently in the long-term study were: depression/withdrawn behavior, weight loss, haircoat abnormalities, increased blood urea nitrogen (BUN), weakness, agitation and diarrhea. Most of the adverse reactions reported were mild and transient.

Serum chemistry and hematology results in the extended use study were consistent with the trends noted during the field study. The mean alanine transaminase (ALT) was above the reference range at the first two quarterly visits, but within the normal reference range (10-100 U/L) through the next two quarterly visits. Mean lymphocyte counts decreased consistently during the study period, to slightly below the reference range (1200-8000 cells/mcL) at the fourth quarterly visit.

Sixteen cats experienced elevated antinuclear antibody (ANA) titers at one or more points during long-term therapy with Felimazole Coated Tablets but the significance was not determined. Eighteen cats died or were euthanized during the extended use study, four of which may have been related to Felimazole Coated Tablets due to the unmasking/acceleration of chronic renal failure. See PRECAUTIONS.

In a foreign field study with 26 cats using a starting dose of 5 mg twice daily (twice the recommended starting dose), one cat was withdrawn due to lethargy, vomiting and facial excoriations. Marked thrombocytopenia was reported in two cats; the platelet count returned to normal in one cat when Felimazole Coated Tablets® (methimazole tablets) were discontinued. Two cats collapsed and died within 12 days of starting Felimazole Coated Tablets at a dose of 5 mg twice daily. Both cats were reported with lethargy, vomiting, anorexia, and bloody diarrhea; one cat also had pallor.

In a second foreign field study with 78 cats using a starting dose of 2.5 mg twice daily, 4 cats were withdrawn due to suspected adverse reactions to Felimazole Coated Tablets including anemia, cholangiohepatitis, excoriations, vomiting, lethargy, jaundice, and anorexia. One cat receiving 2.5 mg three times daily collapsed and died after 8 weeks of treatment. Adverse reactions included pallor, anorexia, dehydration, jaundice, bleeding diathesis, and anemia. The most frequently reported adverse reactions included mild, transient, self-limiting vomiting, lethargy, and anorexia.

If overdosage occurs, stop treatment and give symptomatic and supportive care.

Foreign Market Experience: The following events were reported voluntarily during post-approval use of Felimazole Coated Tablets in foreign markets: facial pruritus, self-induced excoriations of the head and neck, generalized lymphadenopathy, thrombocytopenia, hematemesis, epistaxis, and elevation of serum liver enzymes and bilirubin.

POST APPROVAL EXPERIENCE (revised 2015):

The following adverse events are based on voluntary, post approval reporting. Not all adverse events are reported to FDA/CVM. It is not always possible to reliably estimate the adverse event frequency or establish a causal relationship to product exposure using these data. The following adverse events are listed in decreasing order of reporting frequency: Anorexia, vomiting, head/facial pruritus or edema, depression/lethargy, weight loss, anemia, elevated liver enzymes, skin lesions, elevated BUN, diarrhea, and thrombocytopenia. In some reported cases, the patients recovered after adverse signs were recognized, the drug was withdrawn, and veterinary care was applied. In some cases, death (or euthanasia) has been reported as an outcome of the adverse reactions listed above.

CONTACT INFORMATION:

To report suspected adverse events, for technical assistance or to obtain a copy of the Safety Data Sheet (SDS), contact Dechra at (866) 933-2472.

For additional information about adverse drug experience reporting for animal drugs, contact FDA at 1-888-FDA-VETS, or online at http://www.fda.gov/reportanimalae

CLINICAL PHARMACOLOGY:

Methimazole is an antithyroid drug that acts by blocking the biosynthesis of thyroid hormone in vivo. The primary action is to inhibit binding of iodide to the enzyme thyroid peroxidase, thereby preventing the catalyzed iodination of thyroglobulin and T3 and T4 synthesis.

Felimazole Coated Tablets are well absorbed following oral administration. Maximum plasma concentrations are achieved within 1-1½ hours after dosing and methimazole is rapidly eliminated from the blood (T½ is approximately 3 hours). Administration of Felimazole Coated Tablets in a fasted state enhances absorption.

EFFECTIVENESS:

In a US effectiveness field study with 113 cats, the product was considered effective if both the TT4 concentration was ≤ 4.0 mcg/dL, and the Investigator's clinical assessment documented clinical improvement. Of the 105 evaluable cases, 64 (61%) were considered treatment successes. The decrease in TT4 concentration was significant from the pre-enrollment visit to the Day 42 visit. A TT4 of ≤ 4.0 mcg/dL occurred in 59.1% and 61.9% of cats on Day 21 and Day 42, respectively. Investigators assessed 91.8% and 87.6% of cats as clinically improved on Days 21 and 42, respectively.

In the extended use phase of the US effectiveness field study with 101 cats, effectiveness was based on a combination of Investigator's clinical assessment, maintenance of TT4 concentrations at or near the laboratory reference range of 0.8-4.0 mcg/dL, and the presence or absence of adverse reactions. Mean TT4 concentrations were within or near the laboratory reference range during the first four quarterly visits. At the first quarterly visit, Investigators categorized 80.9% of cats as stable or improved relative to their baseline assessment. By the fourth quarterly visit, 75.8% were deemed to be stable or improved.

The average maintenance dose required in the extended use phase was 2.5 mg twice daily, with a minimum of 2.5 mg per cat and a maximum of 15 mg per cat on a daily basis.

ANIMAL SAFETY:

ANIMAL SAFETY STUDIES: In a 12-week safety study, healthy young cats were dosed with 0, 10, 20, and 30 mg Felimazole Coated Tablets per day, divided into two doses. Cats in all treated groups experienced anorexia, vomiting, loose stool and lethargy. Cats in the 20 and 30 mg/day groups also had facial excoriations, pruritus, and lymphadenopathy. The following hematological changes were seen: neutropenia, lymphopenia, anemia, and thrombocytopenia. The following biochemical changes were seen: increased globulin, increased magnesium, increased blood urea nitrogen, increased creatinine and decreased phosphorus. There was a dose-dependent occurrence of antinuclear antibodies. Most of the clinical pathology changes were mild in nature. One cat dosed with 20 mg/day experienced a six-fold increase in ALT during the study. This cat had loose stool, but was otherwise healthy throughout the study. Hepatomegaly was seen in this cat at necropsy and the histopathological examination was comparable to other treated cats with hepatomegaly and normal ALT.

Gross necropsy findings in all treated groups included hepatomegaly, thymus atrophy and thyroid hyperplasia and darkening. Some treated males had delayed maturation of the testes.

The 30 mg/day dose was poorly tolerated and resulted in the clinical deterioration and euthanasia of four of the six cats in that group. Two of the cats showed signs of immune-mediated hemolytic anemia, thrombocytopenia and severe clinical deterioration. One had been on the drug for 34 days, the other for 9 weeks. The drug was discontinued in a third cat treated with 30 mg/day while it received supportive care.

It was euthanized on day 55 after becoming anorexic. This cat had anemia (HCT 21.6%) and red blood cell agglutination. Necropsy showed inflammation of the muscular layer of the stomach and a small erosion in the stomach. A fourth cat treated with 30 mg/day was euthanized after several days of anorexia when the decision was made to discontinue dosing in this group. All 30 mg/day cats that died had generalized lymphadenopathy. Necropsies revealed reactive lymph nodes and varying degrees of inflammation throughout the body. The remaining 2 cats in the 30 mg/day group were taken off Felimazole Coated Tablets at week 9 and fully recovered.

STORAGE INFORMATION:

Store at controlled room temperature 25°C (77°F) with excursions between 15°-30°C (59°-86°F) permitted. Keep the container tightly closed in order to protect from moisture.

HOW SUPPLIED:

Felimazole Coated Tablets are available in 2.5 mg or 5 mg in bottles containing 100 tablets.

Approved by FDA under NADA # 141-292

Manufactured for:
Dechra Veterinary Products, 7015 College Boulevard, Suite 525, Overland Park, KS 66211 USA
Felimazole is a trademark of Dechra Limited
© 2021, Dechra Limited

Rev. November 2021

21072515

PRINCIPAL DISPLAY PANEL - 2.5 mg Tablet Bottle Carton

2.5 mg

Felimazole®
Coated Tablets
(methimazole tablets)

2.5 mg

For oral use in cats only

CAUTION: Federal law restricts this
drug to use by or on the order of a
licensed veterinarian.

Approved by FDA under
NADA # 141-292

100 tablets

Dechra

PRINCIPAL DISPLAY PANEL - 5 mg Tablet Bottle Carton

5 mg

Felimazole®
Coated Tablets
(methimazole tablets)

5 mg

For oral use in cats only

CAUTION: Federal law restricts this
drug to use by or on the order of a
licensed veterinarian.

Approved by FDA under
NADA # 141-292

100 tablets

Dechra